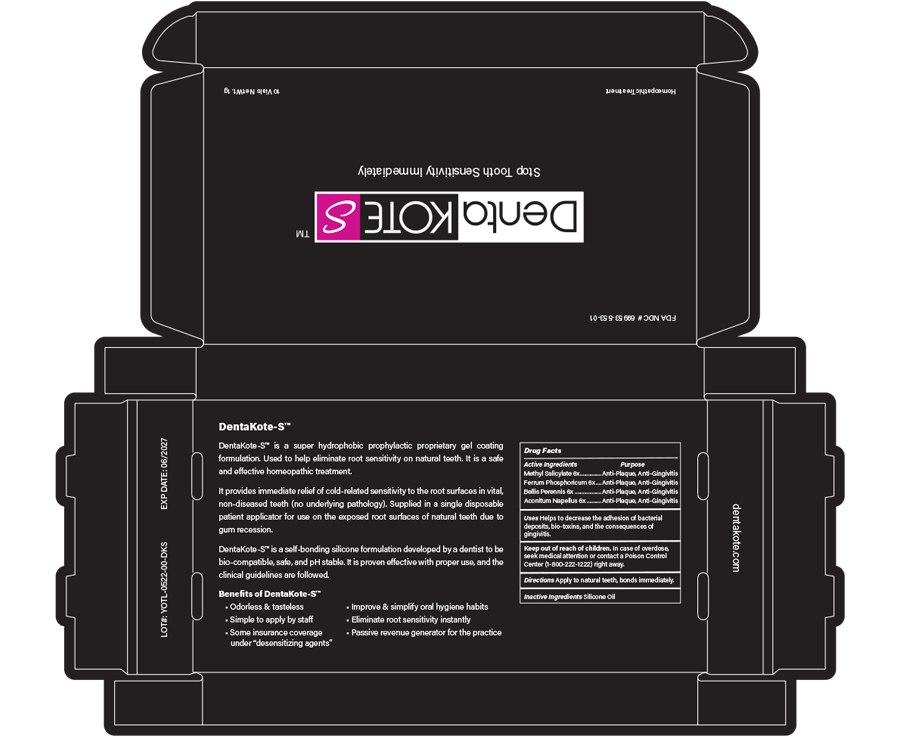 DRUG LABEL: DentaKoteS
NDC: 69953-553 | Form: GEL
Manufacturer: Rapha Pharmaceuticals, Inc.
Category: homeopathic | Type: HUMAN OTC DRUG LABEL
Date: 20230119

ACTIVE INGREDIENTS: METHYL SALICYLATE 6 [hp_X]/6 [hp_X]; ACONITUM NAPELLUS 6 [hp_X]/6 [hp_X]; FERROSOFERRIC PHOSPHATE 6 [hp_X]/6 [hp_X]; BELLIS PERENNIS 6 [hp_X]/6 [hp_X]
INACTIVE INGREDIENTS: DIMETHICONE

ACTIVE INGREDIENTS

Methyl Salicylate 6x, Ferrum Phosphoricum 6x, Bellis Perennis 6x, Aconitum Napellus 6x

PURPOSE

Anti-Plaque, Anti-Gingivitis

USE

Helps to decrease the adhesion of bacterial deposits, bio-toxins, and the consequences of gingivitis.

KEEP OUT OF REACH OF CHILDREN

DIRECTIONS

Apply to natural teeth and dental prosthetics, bonds immediately.

WARNINGS

In case of overdose, seek medical attention or contact a Poison Control Center (1-800-222-1222) right away.

INACTIVE INGREDIENTS

Silicone Oil

OTHER INFORMATION

DentaKoteS™

DentaKote-S™ is a super hydrophobic prophylactic proprietary gel coating formulation. Used to help eliminate root sensitivity on natural teeth. It is a safe and effective homeopathic treatment. It provides immediate relief of cold-related sensitivity to the root surfaces in vital, non-diseased teeth (no underlying pathology). Supplied in a single disposable patient applicator for use on the exposed root surfaces of natural teeth due to gum recession.

DentaKote-S™ is a self-bonding silicone formulation developed by a dentist to be bio-compatible, safe, and pH stable. It is proven effective with proper use, and the clinical guidelines are followed.

Benefits of DentaKoteS™

- Odorless & tasteless
- Improve & simplify oral hygiene habits
- Simple to apply by staff
- Eliminate root sensitivity instantly
- Some insurance coverage under “desensitizing agents”
- Passive revenue generator for the practice